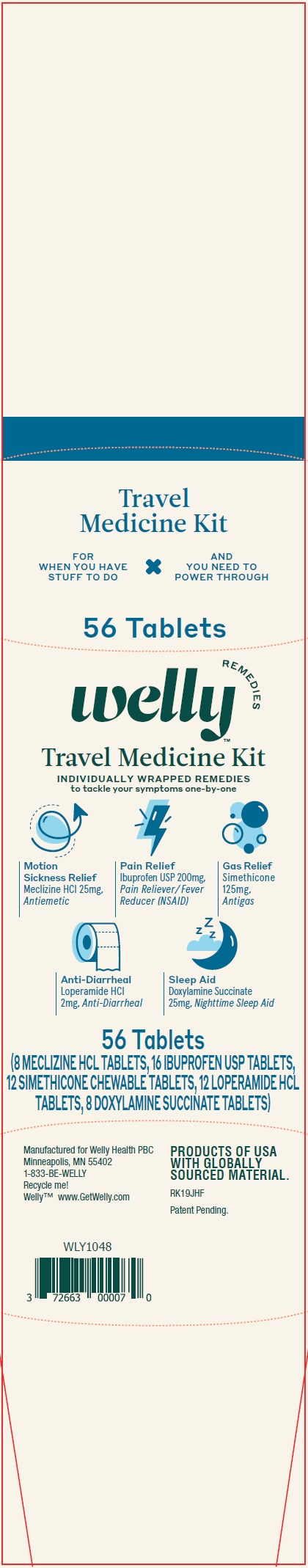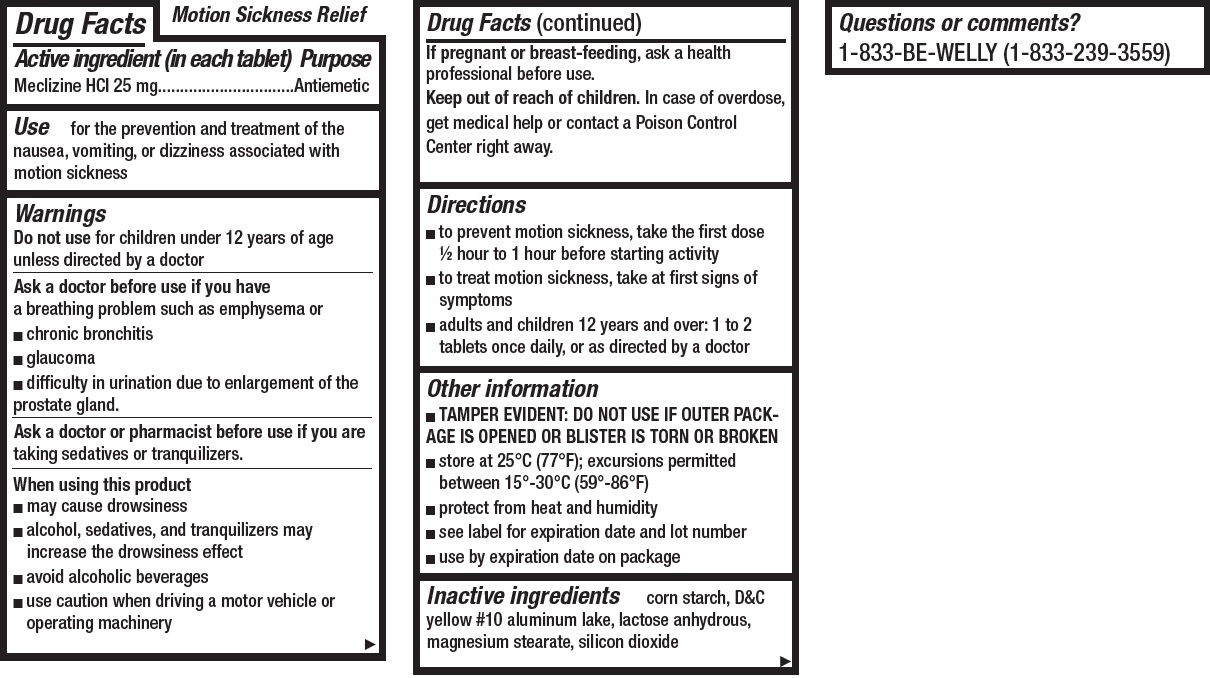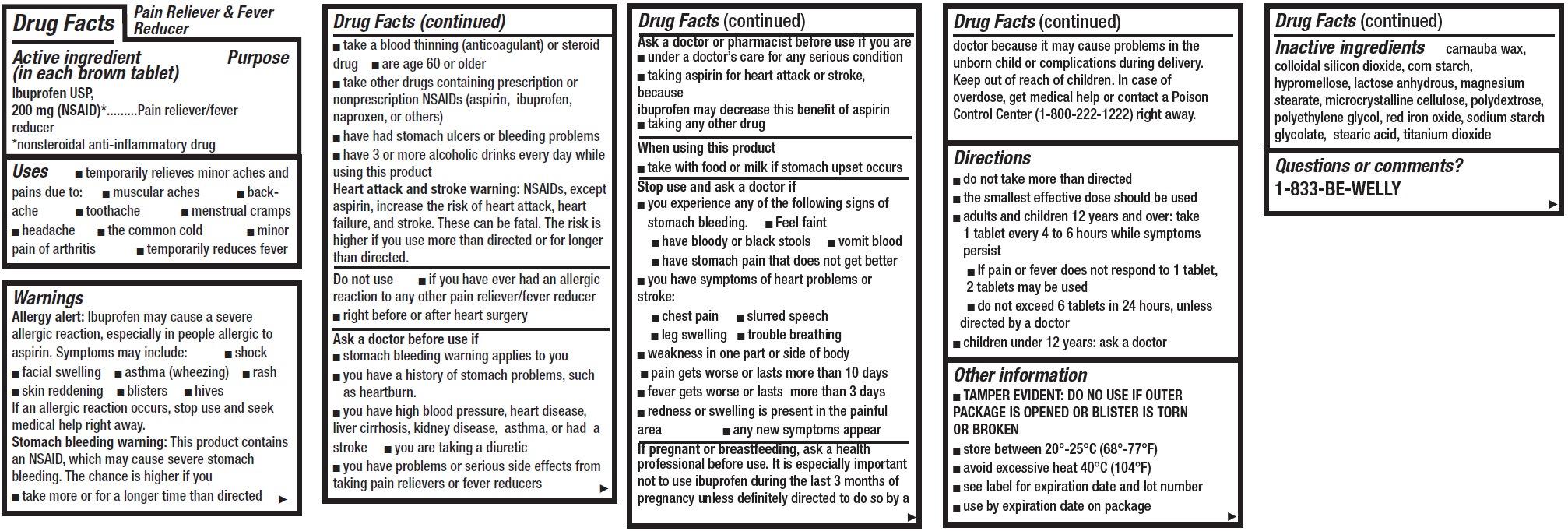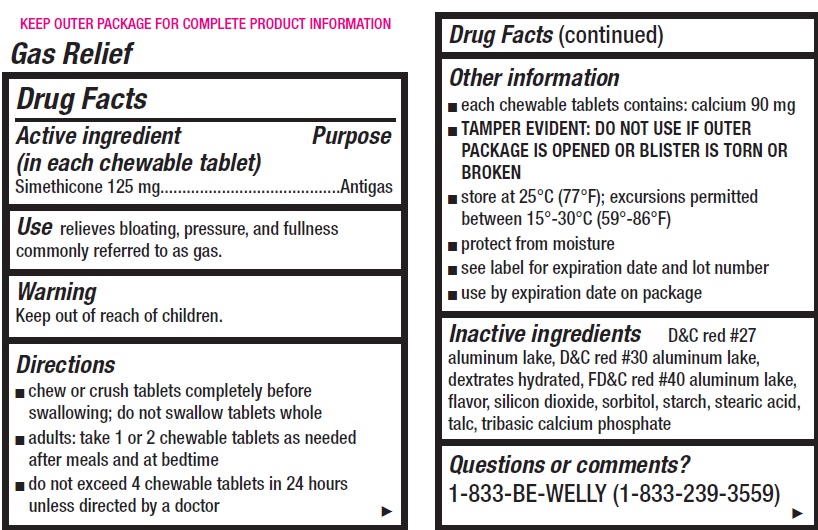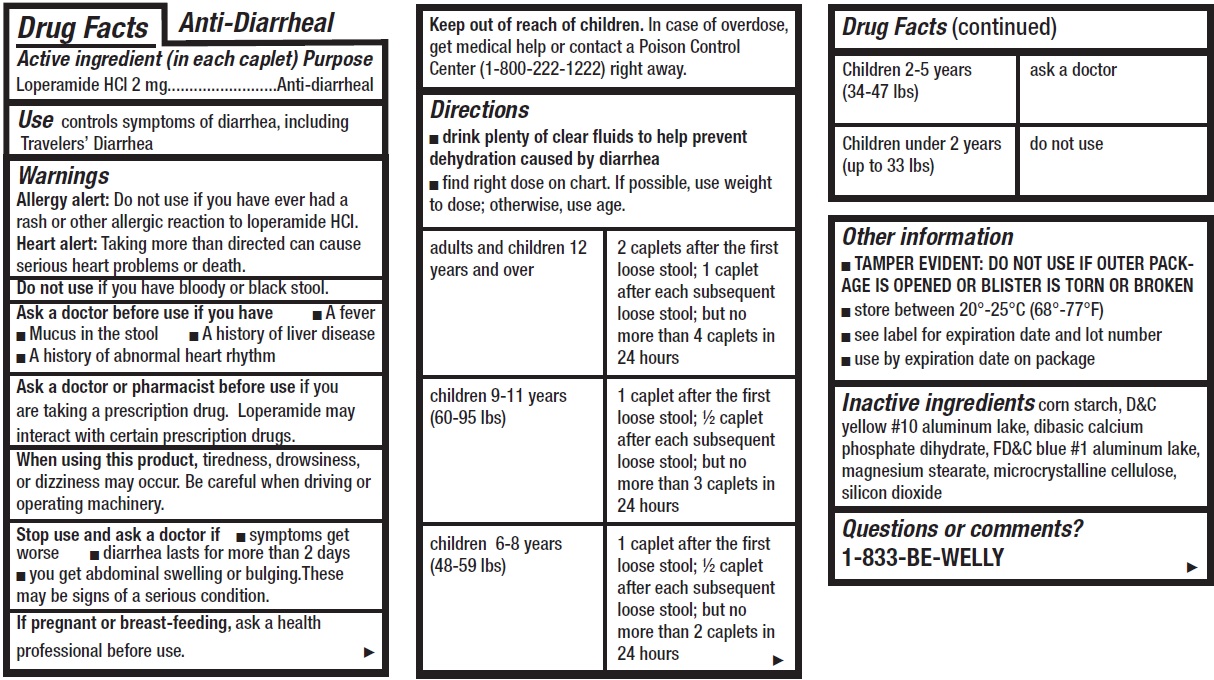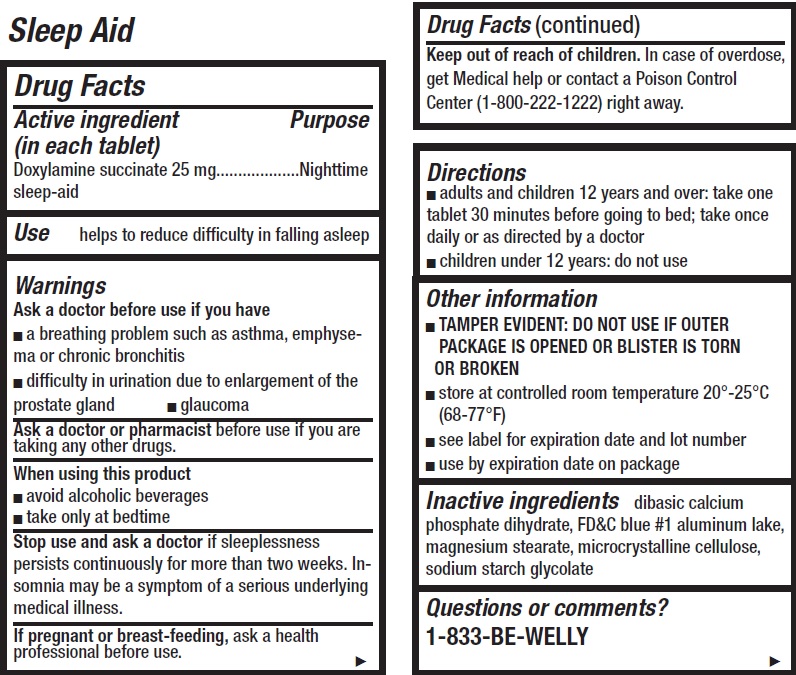 DRUG LABEL: Welly Travel Medicine Kit
NDC: 72663-205 | Form: KIT | Route: ORAL
Manufacturer: Welly Health PBC
Category: otc | Type: HUMAN OTC DRUG LABEL
Date: 20200415

ACTIVE INGREDIENTS: MECLIZINE HYDROCHLORIDE 25 mg/1 1; IBUPROFEN 200 mg/1 1; DIMETHICONE 125 mg/1 1; LOPERAMIDE HYDROCHLORIDE 2 mg/1 1; DOXYLAMINE SUCCINATE 25 mg/1 1
INACTIVE INGREDIENTS: STARCH, CORN; D&C YELLOW NO. 10 ALUMINUM LAKE; ANHYDROUS LACTOSE; MAGNESIUM STEARATE; SILICON DIOXIDE; CARNAUBA WAX; SILICON DIOXIDE; STARCH, CORN; HYPROMELLOSE, UNSPECIFIED; ANHYDROUS LACTOSE; MAGNESIUM STEARATE; MICROCRYSTALLINE CELLULOSE; POLYDEXTROSE; POLYETHYLENE GLYCOL, UNSPECIFIED; FERRIC OXIDE RED; STEARIC ACID; TITANIUM DIOXIDE; D&C RED NO. 27 ALUMINUM LAKE; D&C RED NO. 30; FD&C RED NO. 40; METHYL SALICYLATE; SILICON DIOXIDE; SORBITOL; STEARIC ACID; TALC; TRIBASIC CALCIUM PHOSPHATE; STARCH, CORN; D&C YELLOW NO. 10 ALUMINUM LAKE; DIBASIC CALCIUM PHOSPHATE DIHYDRATE; FD&C BLUE NO. 1 ALUMINUM LAKE; MAGNESIUM STEARATE; MICROCRYSTALLINE CELLULOSE; SILICON DIOXIDE; DIBASIC CALCIUM PHOSPHATE DIHYDRATE; FD&C BLUE NO. 1 ALUMINUM LAKE; MAGNESIUM STEARATE; MICROCRYSTALLINE CELLULOSE

Welly Travel Medicine Kit

Active ingredient (in each tablet)

Meclizine HCI 25 mg

Purpose

Antiemetic

Use

for the prevention and treatment of the nausea, vomiting, or dizziness associated with motion sickness

Warnings

Do not use

for children under 12 years of age unless directed by a doctor

Ask a doctor before use if you have

a breathing problem such as emphysema or

- chronic bronchitis
- glaucoma
- difficulty in urination due to enlargement of the prostate gland.

Ask a doctor or pharmacist before use

if you are taking sedatives or tranquilizers.

When using this product

- may cause drowsiness
- alcohol, sedatives, and tranquilizers may increase the drowsiness effect
- avoid alcoholic beverages
- use caution when driving a motor vehicle or operating machinery

If pregnant or breast-feeding,

ask a health professional before use.

Keep out of reach of children.

In case of overdose, get medical help or contact a Poison Control Center right away.

Directions

- to prevent motion sickness, take the first dose ½ hour to 1 hour before starting activity
- to treat motion sickness, take at first signs of symptoms
- adults and children 12 years and over: 1 to 2 tablets once daily, or as directed by a doctor

Other information

- TAMPER EVIDENT: DO NOT USE IF OUTER PACKAGE IS OPENED OR BLISTER IS TORN OR BROKEN
- store at 25°C (77°F); excursions permitted between 15°-30°C (59°-86°F)
- protect from heat and humidity
- see label for expiration date and lot number
- use by expiration date on package

Inactive ingredients

corn starch, D&C yellow #10 aluminum lake, lactose anhydrous, magnesium stearate, silicon dioxide

Questions or comments?

1-833-BE-WELLY (1-833-239-3559)

Active ingredient (in each brown tablet)

Ibuprofen USP, 200 mg (NSAID)*

*nonsteroidal anti-inflammatory drug

Purpose

Pain reliever/fever reducer

Uses

- temporarily relieves minor aches and pains due to:
- muscular aches
- backache
- toothache
- menstrual cramps
- headache
- the common cold
- minor pain of arthritis
- temporarily reduces fever

Warnings

Allergy alert: Ibuprofen may cause a severe allergic reaction, especially in people allergic to aspirin. Symptoms may include:

- shock
- facial swelling
- asthma (wheezing)
- rash
- skin reddening
- blisters
- hives

If an allergic reaction occurs, stop use and seek medical help right away.

Stomach bleeding warning: This product contains an NSAID, which may cause severe stomach bleeding. The chance is higher if you

- take more or for a longer time than directed
- take a blood thinning (anticoagulant) or steroid drug
- take other drugs containing prescription or nonprescription NSAIDs (aspirin, ibuprofen, naproxen, or others)
- have had stomach ulcers or bleeding problems
- have 3 or more alcoholic drinks every day while using this product
  Heart attack and stroke warning: NSAIDs, except aspirin, increase the risk of heart attack, heart failure, and stroke. These can be fatal. The risk is higher if you use more than directed or for longer than directed.

Do not use

- if you have ever had an allergic reaction to any other pain reliever/fever reducer
- right before or after heart surgery

Ask a doctor before use if

- stomach bleeding warning applies to you
- you have a history of stomach problems, such as heartburn.
- you have high blood pressure, heart disease, liver cirrhosis, kidney disease, asthma, or had a stroke
- you are taking a diuretic
- you have problems or serious side effects from taking pain relievers or fever reducers

Ask a doctor or pharmacist before use if you are

- under a doctor’s care for any serious condition
- taking aspirin for heart attack or stroke, because uprofen may decrease this benefit of aspirin
- taking any other drug

When using this product

- take with food or milk if stomach upset occurs

Stop use and ask a doctor if

- you experience any of the following signs of stomach bleeding.
- Feel faint
- have bloody or black stools
- vomit blood
- have stomach pain that does not get better
- you have symptoms of heart problems or stroke:
- chest pain
- slurred speech
- leg swelling
- trouble breathing
- weakness in one part or side of body
- pain gets worse or lasts more than 10 days
- fever gets worse or lasts more than 3 days
- redness or swelling is present in the painful area
- any new symptoms appear

If pregnant or breastfeeding,

ask a health professional before use. It is especially important not to use ibuprofen during the last 3 months of pregnancy unless definitely directed to do so by a doctor because it may cause problems in the unborn child or complications during delivery.

Keep out of reach of children.

In case of overdose, get medical help or contact a Poison Control Center (1-800-222-1222) right away.

Directions

- do not take more than directed
- the smallest effective dose should be used
- adults and children 12 years and over: take 1 tablet every 4 to 6 hours while symptoms persist
- If pain or fever does not respond to 1 tablet, 2 tablets may be used
- do not exceed 6 tablets in 24 hours, unless directed by a doctor
- children under 12 years: ask a doctor

Other information

- TAMPER EVIDENT: DO NO USE IF OUTER PACKAGE IS OPENED OR BLISTER IS TORN OR BROKEN
- store between 20°-25°C (68°-77°F)
- avoid excessive heat 40°C (104°F)
- see label for expiration date and lot number
- use by expiration date on package

Inactive ingredients

carnauba wax, colloidal silicon dioxide, corn starch, hypromellose, lactose anhydrous, magnesium stearate, microcrystalline cellulose, polydextrose, polyethylene glycol, red iron oxide, sodium starch glycolate, stearic acid, titanium dioxide

Questions or comments?

1-833-BE-WELLY

Active ingredient (in each chewable tablet)

Simethicone 125 mg

Purpose

Antigas

Use

relieves bloating, pressure, and fullness commonly referred to as gas.

Directions

- chew or crush tablets completely before swallowing; do not swallow tablets whole
- adults: take 1 or 2 chewable tablets as needed after meals and at bedtime
- do not exceed 4 chewable tablets in 24 hours unless directed by a doctor

Other information

- each chewable tablets contains: calcium 90 mg
- TAMPER EVIDENT: DO NOT USE IF OUTER PACKAGE IS OPENED OR BLISTER IS TORN OR BROKEN
- store at 25°C (77°F); excursions permitted between 15°-30°C (59°-86°F)
- protect from moisture
- see label for expiration date and lot number
- use by expiration date on package

Inactive ingredients

D&C red #27 aluminum lake, D&C red #30 aluminum lake, dextrates hydrated, FD&C red #40 aluminum lake, flavor, silicon dioxide, sorbitol, starch, stearic acid, talc, tribasic calcium phosphate

Questions or comments?

1-833-BE-WELLY (1-833-239-3559)

Active ingredient (in each caplet)

Loperamide HCI 2 mg

Purpose

Anti-diarrheal

Use

controls symptoms of diarrhea, including Travelers’ Diarrhea

Warnings

Allergy alert: Do not use if you have ever had a rash or other allergic reaction to loperamide HCI.
Heart alert: Taking more than directed can cause serious heart problems or death.

Do not use

you have bloody or black stool.

Ask a doctor before use if you have

- A fever
- Mucus in the stool
- A history of liver disease
- A history of abnormal heart rhythm

Ask a doctor or pharmacist before use

if you are taking a prescription drug. Loperamide may interact with certain prescription drugs.

When using this product,

tiredness, drowsiness, or dizziness may occur. Be careful when driving or operating machinery.

Stop use and ask a doctor if

- symptoms get worse
- diarrhea lasts for more than 2 days
- you get abdominal swelling or bulging.These may be signs of a serious condition.

If pregnant or breast-feeding,

ask a health professional before use.

Keep out of reach of children.

In case of overdose, get medical help or contact a Poison Control Center (1-800-222-1222) right away.

Directions

- drink plenty of clear fluids to help prevent dehydration caused by diarrhea
- find right dose on chart. If possible, use weight to dose; otherwise, use age.

adults and children 12 years and over | 2 caplets after the first loose stool; 1 caplet after each subsequent loose stool; but no more than 4 caplets in 24 hours
children 9-11 years (60-95 lbs) | 1 caplet after the first loose stool; ½ caplet after each subsequent loose stool; but no more than 3 caplets in 24 hours
children 6-8 years (48-59 lbs) | 1 caplet after the first loose stool; ½ caplet after each subsequent loose stool; but no more than 2 caplets in 24 hours
Children 2-5 years (34-47 lbs) | ask a doctor
Children under 2 years (up to 33 lbs) | do not use

Other information

- TAMPER EVIDENT: DO NOT USE IF OUTER PACKAGE IS OPENED OR BLISTER IS TORN OR BROKEN
- store between 20°-25°C (68°-77°F)
- see label for expiration date and lot number
- use by expiration date on package

Inactive ingredients

corn starch, D&C yellow #10 aluminum lake, dibasic calcium phosphate dihydrate, FD&C blue #1 aluminum lake, magnesium stearate, microcrystalline cellulose, silicon dioxide

Questions or comments?

1-833-BE-WELLY

Active ingredient (in each tablet)

Doxylamine succinate 25 mg

Purpose

Nighttime sleep-aid

Use

helps to reduce difficulty in falling asleep

Warnings

Ask a doctor before use if you have

- a breathing problem such as asthma, emphysema or chronic bronchitis
- difficulty in urination due to enlargement of the prostate gland
- glaucoma

Ask a doctor or pharmacist before

use if you are taking any other drugs.

When using this product

- avoid alcoholic beverages
- take only at bedtime

Stop use and ask a doctor

if sleeplessness persists continuously for more than two weeks. Insomnia may be a symptom of a serious underlying medical illness.

If pregnant or breast-feeding,

ask a health professional before use.

Keep out of reach of children.

In case of overdose, get Medical help or contact a Poison Control Center (1-800-222-1222) right away.

Directions

- adults and children 12 years and over: take one tablet 30 minutes before going to bed; take once daily or as directed by a doctor
- children under 12 years: do not use

Other information

- TAMPER EVIDENT: DO NOT USE IF OUTER PACKAGE IS OPENED OR BLISTER IS TORN OR BROKEN
- store at controlled room temperature 20°-25°C (68-77°F)
- see label for expiration date and lot number
- use by expiration date on package

Inactive ingredients

dibasic calcium phosphate dihydrate, FD&C blue #1 aluminum lake, magnesium stearate, microcrystalline cellulose, sodium starch glycolate

Questions or comments?

1-833-BE-WELLY